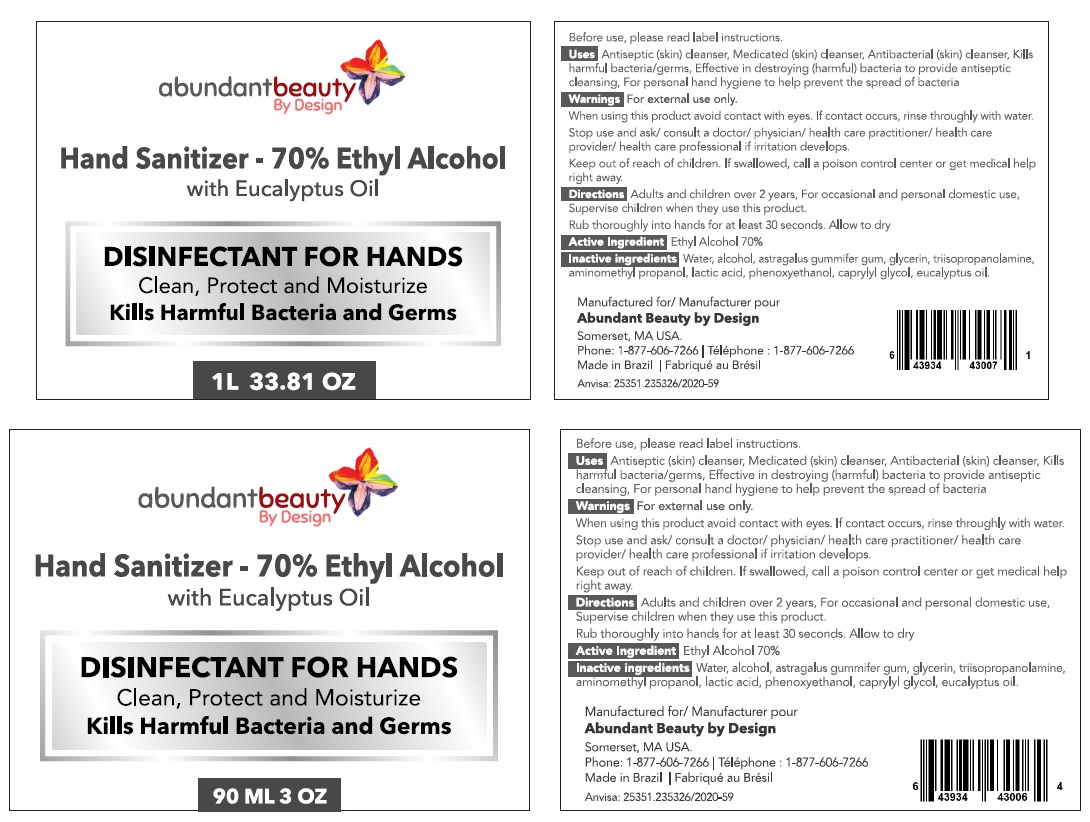 DRUG LABEL: Abundant Beauty by Design - Hand Sanitizer 70%
NDC: 78667-667 | Form: GEL
Manufacturer: GYP INDUSTRIA DE COSMETICOS EIRELI
Category: otc | Type: HUMAN OTC DRUG LABEL
Date: 20200610

ACTIVE INGREDIENTS: ALCOHOL 70 mL/100 mL
INACTIVE INGREDIENTS: WATER; TRAGACANTH; GLYCERIN; TRIISOPROPANOLAMINE; AMINOMETHYLPROPANOL; LACTIC ACID, UNSPECIFIED FORM; PHENOXYETHANOL; CAPRYLYL GLYCOL; EUCALYPTUS OIL

abundant beauty By Design Hand Sanitizer

Before use, please read label instructions.

Active Ingredient Ethyl Alcohol 70%

Purpose Antiseptic

INDICATIONS AND USAGE

Uses Antiseptic (skin) cleanser, Medicated (skin) cleanser, Antibacterial (skin) cleanser, Kills harmful bacteria/germs, Effective in destroying (harmful) bacteria to provide antiseptic cleansing, For personal hand hygiene to help prevent the spread of bacteria

Warnings For external use only.

When using this product avoid contact with eyes. If contact occurs, rinse thoroughly with water.

Stop use and ask/ consult a doctor/ physician/ health care practitioner/ health care provider/ health care professional if irritation develops.

Keep out of reach of children. If swallowed, call a poison control center or get medical help right away.

DOSAGE AND ADMINISTRATION

Directions Adults and children over 2 years, For occasional and personal domestic use, Supervise children when they use this product.

Rub thoroughly into hands for at least 30 seconds. Allow to dry

INACTIVE INGREDIENT

Inactive Ingredients Water, astragalus gummifier gum, glycerin, triisopropanolamine, aminomethyl propanol, lactic acid, phenoxyethanol, caprylyl glycol, eucalyptus oil.

with Eucalyptus Oil

DISINFECTANT FOR HANDS

Clean, Protect and Moisturize

Kills Harmful Bacteria and Germs

Manufactured for/Manufacturer pour

Abundant Beauty by Design

Somerset, MA USA.

Phone: 1-877-606-7266 | Téléphone : 1-877-606-7266

Made in Brazil | Fabriqué au Brésil

Anvisa: 25351.235326/2020-59